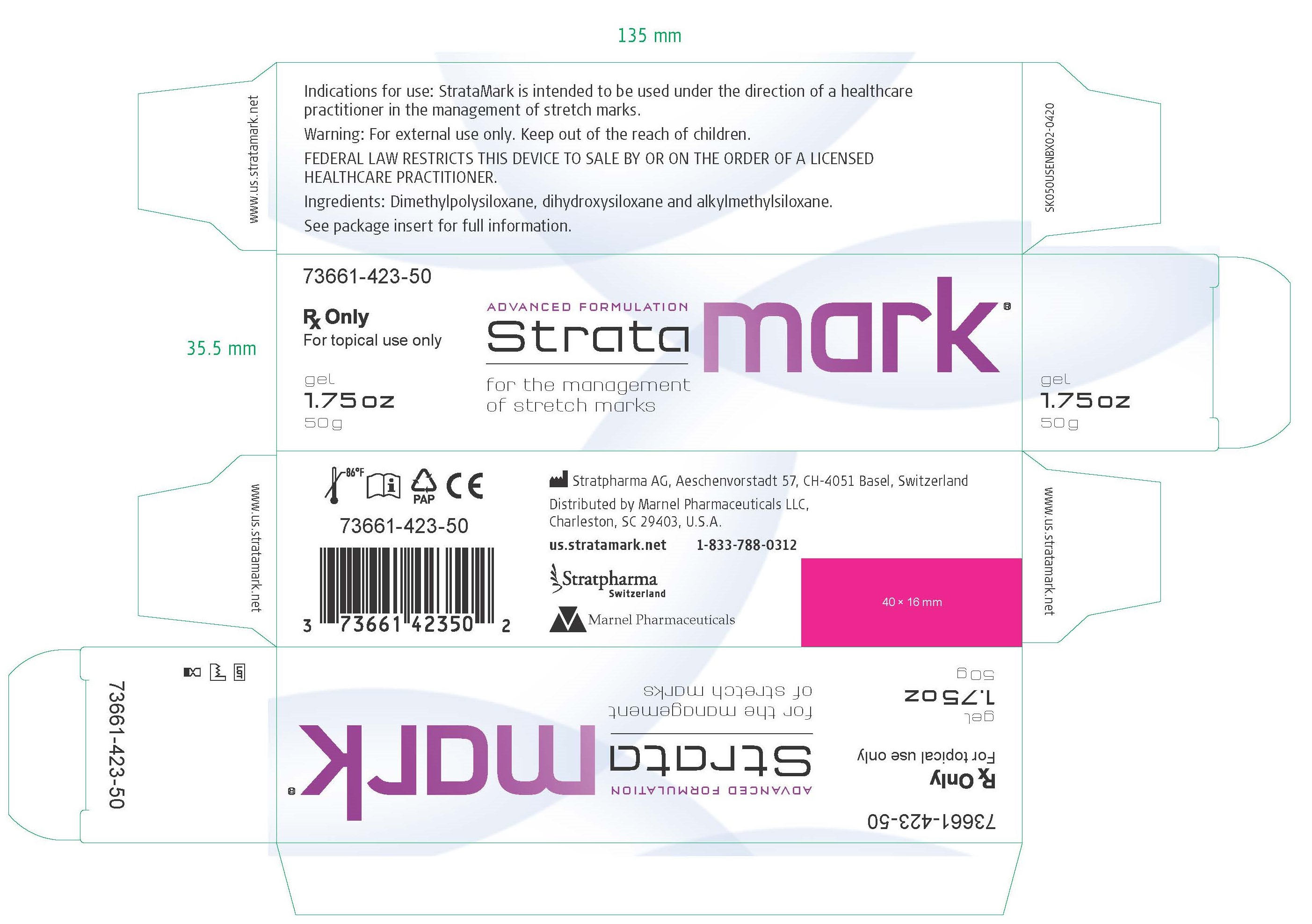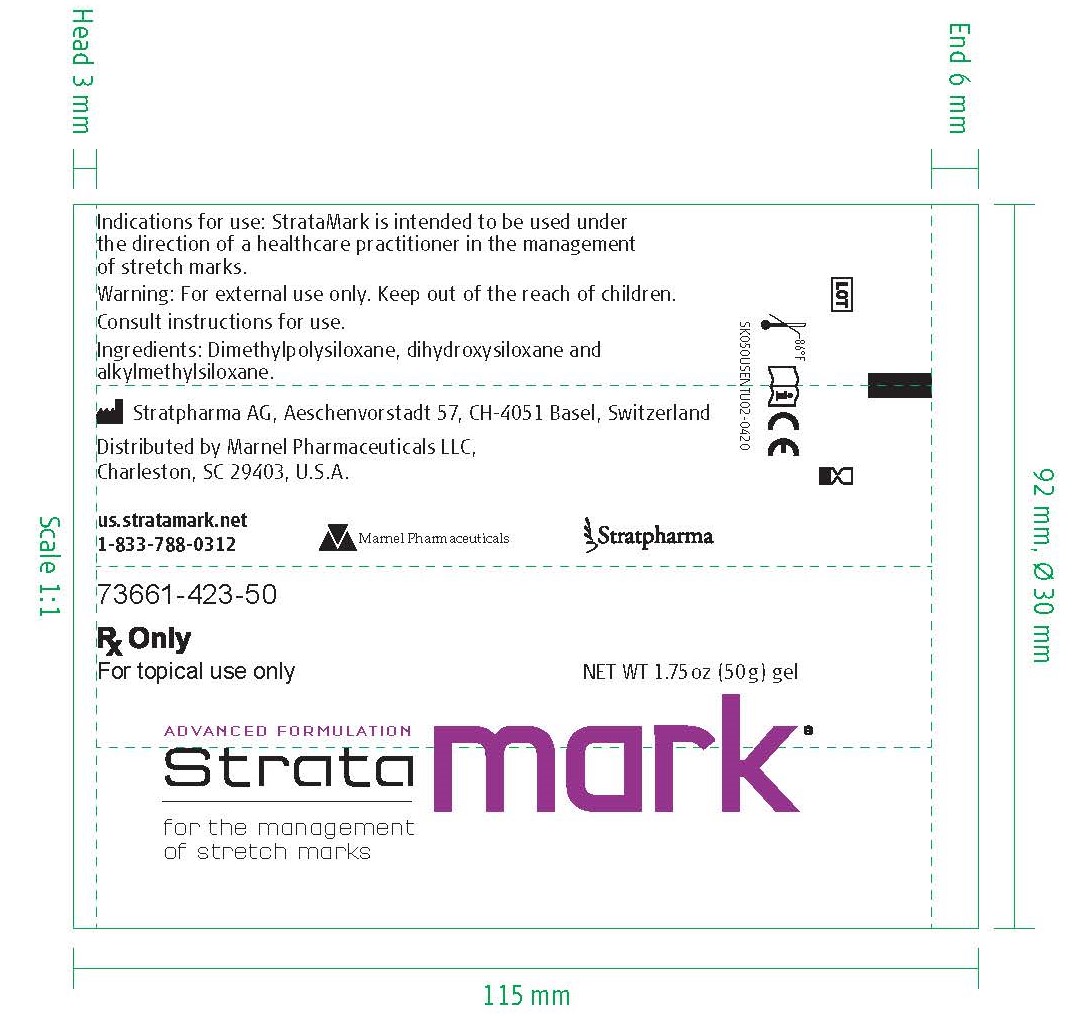 DRUG LABEL: StrataMark
NDC: 73661-423
Manufacturer: Marnel Pharmaceuticals, Inc.
Category: other | Type: MEDICAL DEVICE
Date: 20200711
INACTIVE INGREDIENTS: DIMETHICONE; DIMETHICONOL (2000 CST); CAPRYLYL TRISILOXANE

StrataMark

WARNINGS AND PRECAUTIONS

Rx Only

For topical use only

Federal Law restricts this device to sale by or on the order of a licensed healthcare practitioner.

[EN]Description

StrataMark is a rapidly drying, non-sticky, transparent gel formulation for the management of Striae Distensae (stretch marks).

When used as directed, StrataMark dries to form a thin, flexible and protective layer, that is gas permeable and water-proof which hydrates and protects stretch marks, allowing the skin to normalize the collagen synthesis cycle.

StrataMark is suitable for all areas of the skin, including exposed and sensitive areas, as well as large areas of the body (i.e. buttocks, abdomen, thighs, breasts and back).

INDICATIONS AND USAGE

Indication for use

StrataMark is intended to be used under the direction of healthcare practitioners in the management of stretch marks.

StrataMark is indicated for the management of all types of stretch marks, particularly those covering a wide surface area, resulting from pregnancy, adolescent growth spurts, weight gain or loss, or bodybuilding.

StrataMark is indicated to soften and flatten stretch marks, reduce redness and discoloration associated with stretch marks as well as to relieve the itching and discomfort of stretch marks.

It contains no alcohols, parabens or fragrances.

StrataMark is suitable for pregnant women, breastfeeding mothers, children and people with sensitive skin.

StrataMark is intended for single patient use.

INDICATIONS AND USAGE

Directions for use

On the first use of 1.75 oz (50g) tubes, remove the cap, then the protective seal and close with the cap after use.

Ensure that the skin is clean and dry.

Apply a very thin layer of StrataMark to the relevant areas with the fingertips and distribute evenly to form a very thin layer and allow the gel to dry.

When applied, StrataMark should be dry in 5-6 minutes.

If it takes longer to dry you have probably applied too much. Gently remove the excess with a clean tissue or gauze and allow the drying process to continue.

Once dry, StrataMark can be covered with undergarments, sunscreens or cosmetics.

StrataMark should be applied once per day or as advised by your physician.

For best results StrataMark should be maintained in continuous contact with the skin (24 hours a day/7 days a week).

PATIENT COUNSELING INFORMATION

How much StrataMark do I need?

StrataMark gel is an advanced formulation that requires substantially less product per application than typical creams or gels.

StrataMark 1.75 oz (50g) is enough to treat an area of 12x12 inch (30x30cm) for 30 days.

Warning

- For external use only.
- StrataMark should not be applied to third degree burns or to open wounds.
- StrataMark should not be placed in contact with eyes.
- StrataMark should not be applied over other skin treatments without the advice of your physician.
- StrataMark may stain clothing if not completely dry. If staining occurs, dry cleaning should be able to remove it without damaging the fabric.
- For correct storage please reclose the tube tightly with the cap.
- If irritation occurs, discontinue use and consult your physician.
- Keep out of the reach of children.
- Do not use after the expiration (EXP) date printed on the tube. The expiration (EXP) date does not change once the tube has been opened.
- Do not use if the tube is damaged.

Contraindications:

Do not administer to patients with known hypersensitivity to the ingredients of this product.

Ingredients: Dimethylpolysiloxane, dihydroxysiloxane and alkylmethylsiloxane.

How supplied:

StrataMark 1.75 oz (50g) tube

Product identification code:

73661-423-50